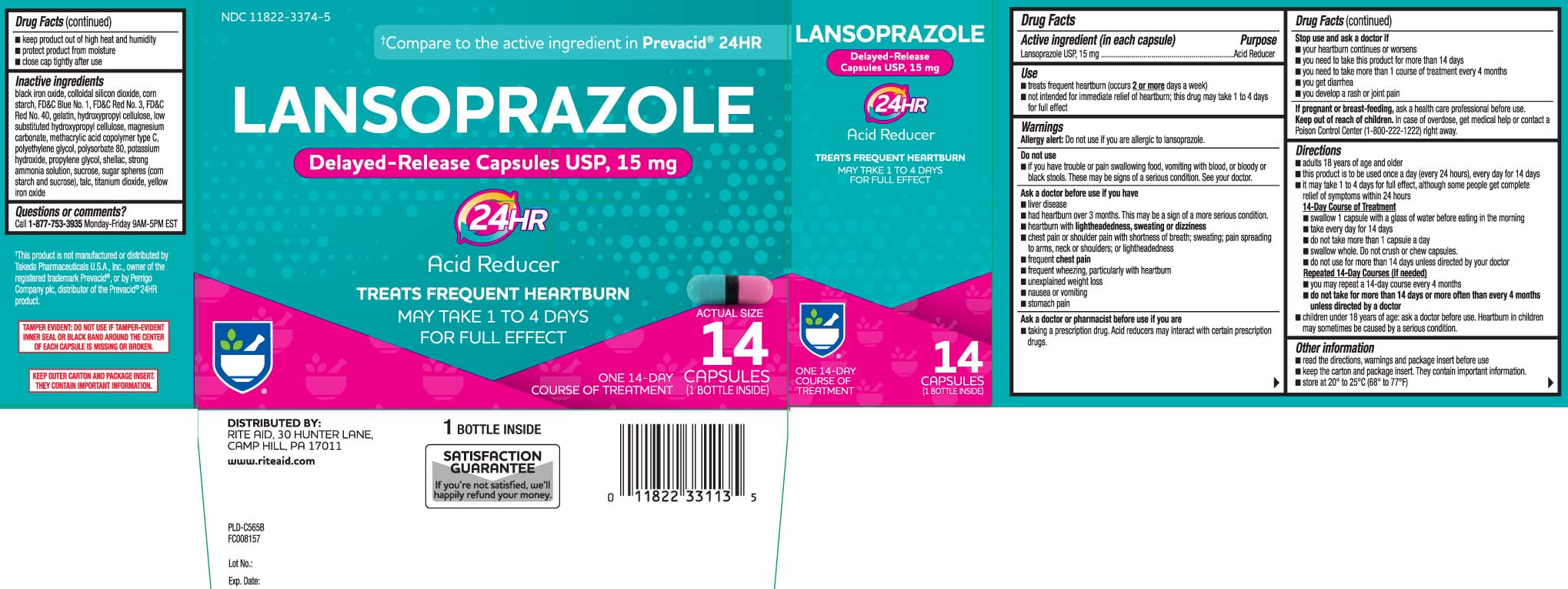 DRUG LABEL: Lansoprazole
NDC: 11822-3374 | Form: CAPSULE, DELAYED RELEASE
Manufacturer: Rite Aid Corporation
Category: otc | Type: HUMAN OTC DRUG LABEL
Date: 20250825

ACTIVE INGREDIENTS: LANSOPRAZOLE 15 mg/1 1
INACTIVE INGREDIENTS: FERROSOFERRIC OXIDE; SILICON DIOXIDE; STARCH, CORN; FD&C BLUE NO. 1; FD&C RED NO. 3; FD&C RED NO. 40; GELATIN; HYDROXYPROPYL CELLULOSE, UNSPECIFIED; HYDROXYPROPYL CELLULOSE, LOW SUBSTITUTED; MAGNESIUM CARBONATE; METHACRYLIC ACID AND ETHYL ACRYLATE COPOLYMER; POLYETHYLENE GLYCOL, UNSPECIFIED; POLYSORBATE 80; SHELLAC; AMMONIA; SUCROSE; TALC; TITANIUM DIOXIDE; FERRIC OXIDE YELLOW

DRUG FACTS

Active ingredient (in each capsule)

Lansoprazole USP, 15 mg

Purpose

Acid Reducer

Use

- treats frequent heartburn (occurs 2 or more days a week)
- not intended for immediate relief of heartburn; this drug may take 1 to 4 days for full effect

Warnings

Allergy alert: Do not use if you are allergic to lansoprazole.

Do not use

- if you have trouble or pain swallowing food, vomiting with blood, or bloody or black stools. These may be signs of a serious condition. See your doctor.

Ask a doctor before use if you have

- liver disease
- had heartburn over 3 months. This may be a sign of a more serious condition.
- heartburn with lightheadedness, sweating or dizziness
- chest pain or shoulder pain with shortness of breath; sweating; pain spreading to arms, neck or shoulders; or lightheadedness
- frequent chest pain
- frequent wheezing, particularly with heartburn
- unexplained weight loss
- nausea or vomiting
- stomach pain

Ask a doctor or pharmacist before use if you are

- taking a prescription drug. Acid reducers may interact with certain prescription drug

Stop use and ask a doctor if

- your heartburn continues or worsens
- you need to take this product for more than 14 days
- you need to take more than 1 course of treatment every 4 months
- you get diarrhea
- you develop a rash or joint pain

If pregnant or breast-feeding,

ask a health professional before use.

Keep out of reach of children.

In case of overdose, get medical help or contact a Poison Control Center (1-800-222-1222) right away.

Directions

- adults 18 years of age and older
- this product is to be used once a day (every 24 hours), every day for 14 days
- it may take 1 to 4 days for full effect, although some people get complete relief of symptoms within 24 hours

14-Day Course of Treatment

- swallow 1 capsule with a glass of water before eating in the morning
- take every day for 14 days
- do not take more than 1 capsule a day
- swallow whole. Do not crush or chew capsules.
- do not use for more than 14 days unless directed by your doctor

Repeated 14-Day Courses (if needed)

- you may repeat a 14-day course every 4 months
- do not take for more than 14 days or more often than every 4 months unless directed by a doctor
- children under 18 years of age: ask a doctor before use. Heartburn in children may sometimes be caused by a serious condition.

Other information

- read the directions, warnings and package insert before use
- keep the carton and package insert. They contain important information.
- store at 20°-25°C (68°-77°F)
- keep product out of high heat and humidity
- protect product from moisture
- close cap tightly after use

Inactive ingredients

black iron oxide,colloidal silicon dioxide, corn starch, FD&C Blue #1, FD&C red #3, FD&C red #40, gelatin, hydroxypropyl cellulose, low substituted hydroxypropyl cellulose, magnesium carbonate, methacrylic acid copolymer type C, polyethylene glycol, polysorbate 80, potassium hydroxide, propylene glycol, shellac, strong ammonia solution, sucrose, sugar spheres (corn starch and sucrose), talc, titanium dioxide, yellow iron oxide

Questions or comments?

Call 1-877-753-3935 Monday-Friday 9AM-5PM EST

Principal Display Panel

†Compare to the active ingredient in Prevacid® 24HR*

LANSOPRAZOLE

Delayed-Release Capsules USP, 15 mg

24HR

Acid Reducer

TREATS FREQUENT HEARTBURN

MAY TAKE 1 TO 4 DAYS FOR FULL EFFECT

CAPSULES

†This product is not manufactured or distributed by Takeda Pharmaceuticals U.S.A., Inc., owner of the registered trademark Prevacid®, or by Perrigo Company plc, distributor of the Prevacid® 24HR product.

TAMPER EVIDENT: DO NOT USE IF TAMPER-EVIDENT INNER SEAL OR BLACK BAND AROUND THE CENTER OF EACH CAPSULES IS BROKEN OR MISSING.

KEEP OUTER CARTON AND PACKAGE INSERT. THEY CONTAIN IMPORTANT INFORMATION.

DISTRIBUTED BY:

RITE AID, 30 HUNTER LANE,

CAMP HILL, PA 17011

www.riteaid.com

Package Label

RITE AID Acid Reducer